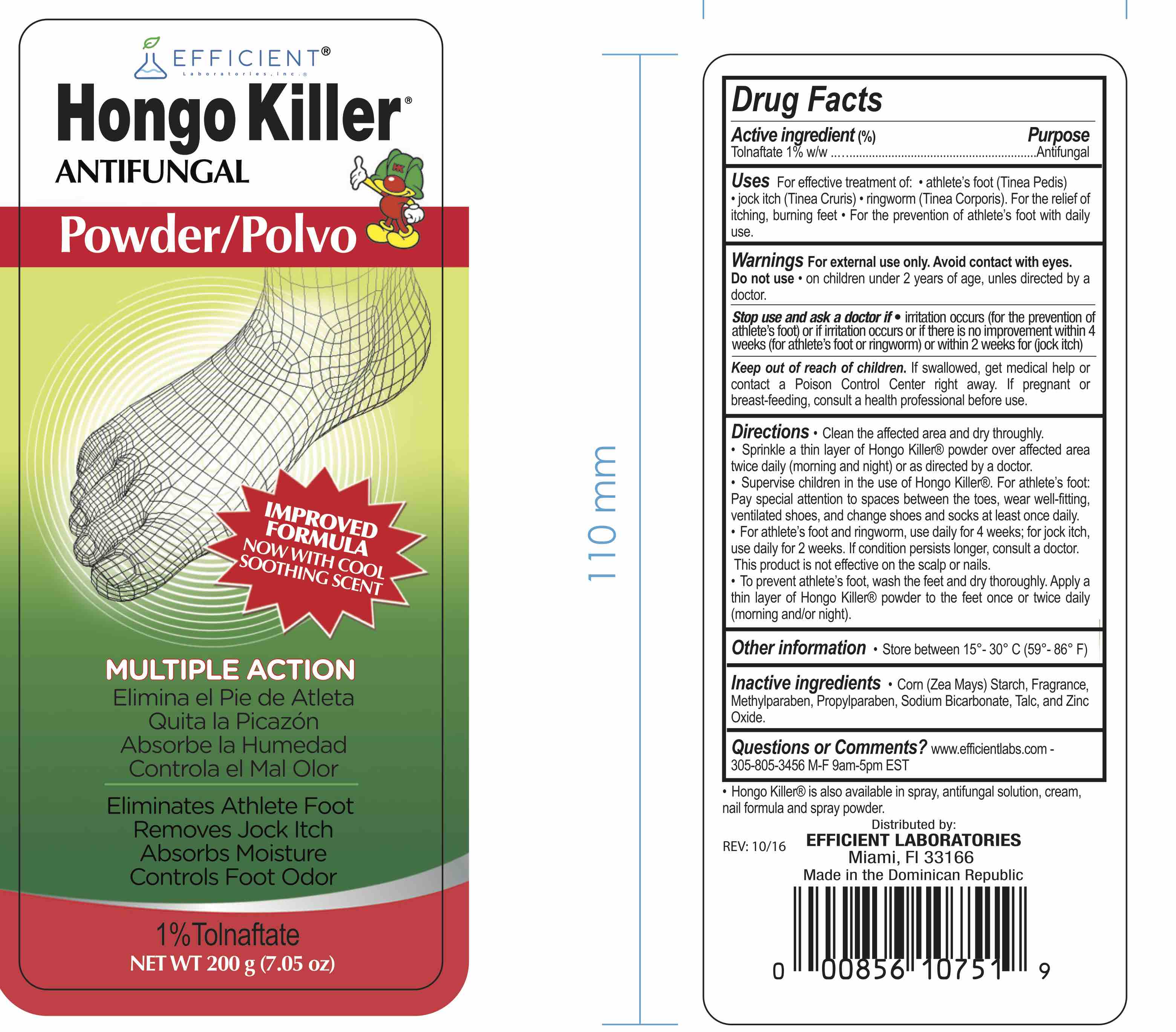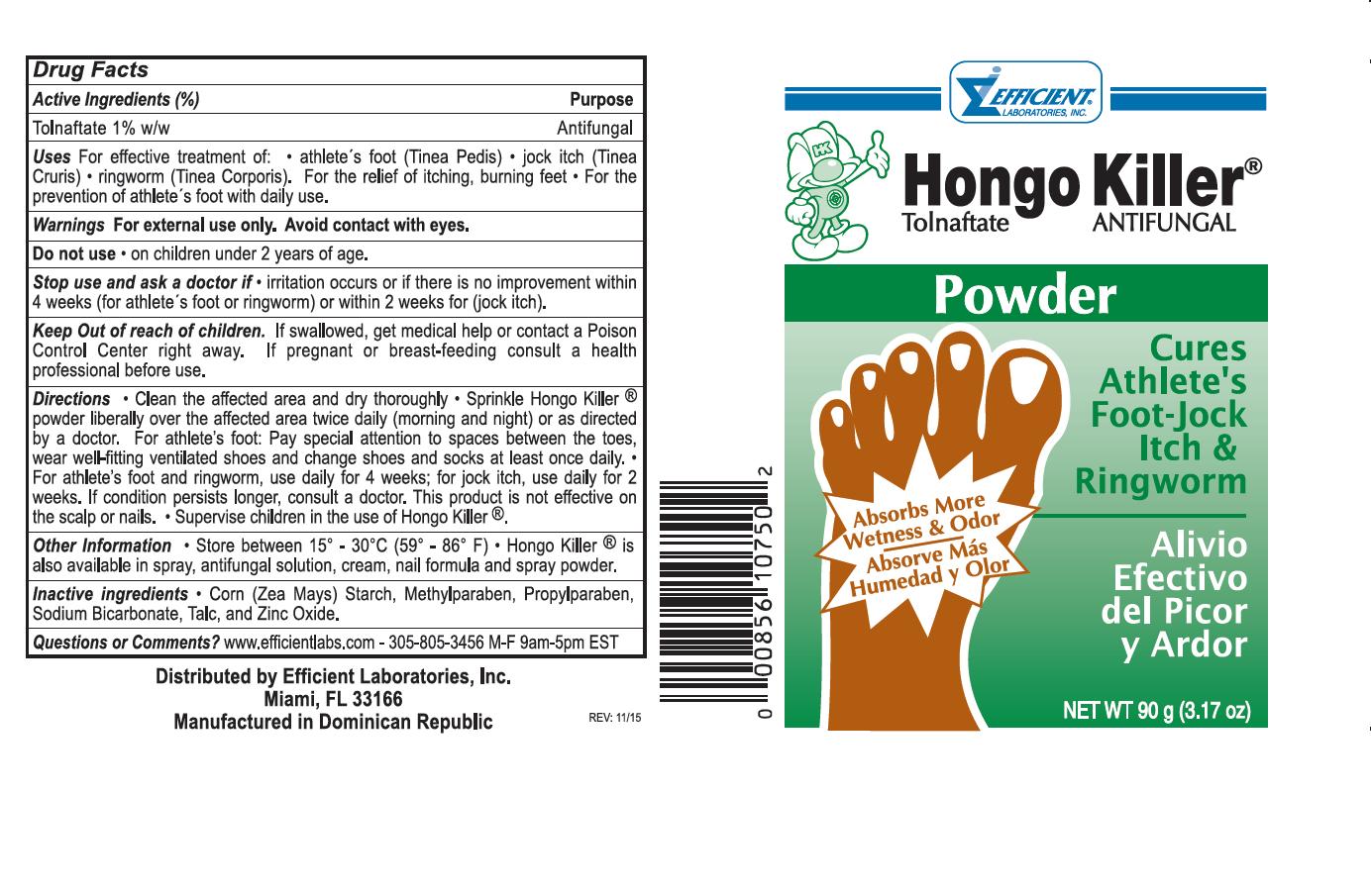 DRUG LABEL: Hongo Killer
NDC: 58593-288 | Form: POWDER
Manufacturer: Efficient Laboratories Inc
Category: otc | Type: HUMAN OTC DRUG LABEL
Date: 20251014

ACTIVE INGREDIENTS: TOLNAFTATE 1 g/100 g
INACTIVE INGREDIENTS: STARCH, CORN; METHYLPARABEN; PROPYLPARABEN; SODIUM BICARBONATE; TALC; ZINC OXIDE

Drug Facts

Active Ingredients: Purpose

Tolnaftate 1% W/W........................ Antifungal

Uses

For effective treatment of:

- athlete's foot (tinea pedis)
- jock itch (Tinea Cruris)
- ringworm (tinea corporis)

For the relief of itching, burning feet.
For the prevention of athlete's foot with daily use

Purpose

Antifungal

Warnings

For external use only. Avoid contact with eyes.

Do not use on children under 2 years of age

Stop use and ask a doctor if irritation occurs or if there's no improvement within 4 weeks (for athlete's foot or ringworm) or within 2 weeks for jock itch.

Keep out of reach of children. If swallowed, get medical help or contact a Poison Control Center right away. If pregnant or breast-feeding consult a health professional before use.

Directions

- clean the affected area and dry thoroughly
- Sprinkle Hongo Killer powder liberally over the affected area twice daily (morning and night) or as direct by doctor
- For athlete's foot: pay special attention to spaces between the toes. Wear well-fitting, ventilated shoes and change shoes and socks at least once daily
- For athlete's foot and ringworm, use daily for 4 weeks; for jock itch, use daily for 2 weeks. If condition persists longer, consult a doctor. This prodcut is not effective on scalp or nails.
- Supervise children in the use of Hongo Killer

Questions or comments?

www.efficientlabs.com

Please Call 305-805-3456 (M-F 9:00-5:00 pm EST)

INACTIVE INGREDIENT

Inactive ingredients Corn (Zea Mays) Starch, Methylparaben, Propylparaben, Sodium Bicardbonate, Talc and Zinc Oxide.